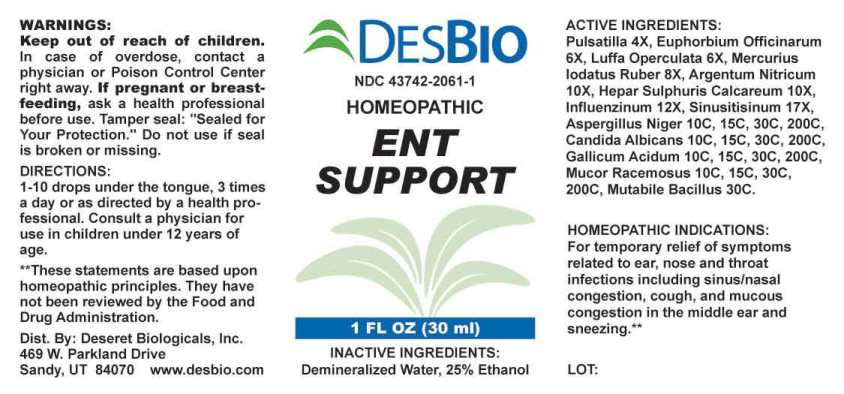 DRUG LABEL: ENT Support
NDC: 43742-2061 | Form: LIQUID
Manufacturer: Deseret Biologicals, Inc.
Category: homeopathic | Type: HUMAN OTC DRUG LABEL
Date: 20240115

ACTIVE INGREDIENTS: PULSATILLA PRATENSIS WHOLE 4 [hp_X]/1 mL; EUPHORBIA RESINIFERA RESIN 6 [hp_X]/1 mL; LUFFA OPERCULATA FRUIT 6 [hp_X]/1 mL; MERCURIC IODIDE 8 [hp_X]/1 mL; SILVER NITRATE 10 [hp_X]/1 mL; CALCIUM SULFIDE 10 [hp_X]/1 mL; INFLUENZA A VIRUS A/VICTORIA/2570/2019 IVR-215 (H1N1) ANTIGEN (UV, FORMALDEHYDE INACTIVATED) 12 [hp_X]/1 mL; INFLUENZA A VIRUS A/DARWIN/9/2021 IVR-228 (H3N2) ANTIGEN (UV, FORMALDEHYDE INACTIVATED) 12 [hp_X]/1 mL; INFLUENZA B VIRUS B/AUSTRIA/1359417/2021 BVR-26 ANTIGEN (UV, FORMALDEHYDE INACTIVATED) 12 [hp_X]/1 mL; INFLUENZA B VIRUS B/PHUKET/3073/2013 ANTIGEN (UV, FORMALDEHYDE INACTIVATED) 12 [hp_X]/1 mL; SINUSITISINUM 17 [hp_X]/1 mL; ASPERGILLUS NIGER VAR. NIGER 10 [hp_C]/1 mL; CANDIDA ALBICANS 10 [hp_C]/1 mL; GALLIC ACID MONOHYDRATE 10 [hp_C]/1 mL; MUCOR RACEMOSUS 10 [hp_C]/1 mL; ESCHERICHIA COLI 30 [hp_C]/1 mL
INACTIVE INGREDIENTS: WATER; ALCOHOL

DRUG FACTS:

ACTIVE INGREDIENTS:

Pulsatilla (Pratensis) 4X, Euphorbium Officinarum 6X, Luffa Operculata 6X, Mercurius Iodatus Ruber 8X, Argentum Nitricum 10X, Hepar Sulphuris Calcareum 10X, Influenzinum (2022-2023) 12X, Sinusitisinum 17X, Aspergillus Niger 10C, 15C, 30C, 200C, Candida Albicans 10C, 15C, 30C, 200C, Gallicum Acidum 10C, 15C, 30C, 200C, Mucor Racemosus 10C, 15C, 30C, 200C, Mutabile Bacillus (Bach) 30C.

HOMEOPATHIC INDICATIONS:

For temporary relief of symptoms related to ear, nose and throat infections including sinus/nasal congestion, cough, and mucous congestion in the middle ear and sneezing.**

**These statements are based upon homeopathic principles. They have not been reviewed by the Food and Drug Administration.

WARNINGS:

Keep out of reach of children. In case of overdose, contact a physician or Poison Control Center right away.

If pregnant or breast-feeding, ask a health professional before use.

Tamper seal: "Sealed for Your Protection." Do not use if seal is broken or missing.

Keep out of reach of children. In case of overdose, contact a physician or Poison Control Center right away.

DIRECTIONS:

1-10 drops under the tongue, 3 times a day or as directed by a health professional. Consult a physician for use in children under 12 years of age.

HOMEOPATHIC INDICATIONS:

For temporary relief of symptoms related to ear, nose and throat infections including sinus/nasal congestion, cough, and mucous congestion in the middle ear and sneezing.**

**These statements are based upon homeopathic principles. They have not been reviewed by the Food and Drug Administration.

INACTIVE INGREDIENTS:

Demineralized Water, 25% Ethanol

QUESTIONS:

Dist. By: Deseret Biologicals, Inc.

469 W. Parkland Drive

Sandy, UT 84070 www.desbio.com

PACKAGE LABEL DISPLAY:

DESBIO

NDC 43742-2061-1

HOMEOPATHIC

ENT

SUPPORT

1 FL OZ (30 ml)